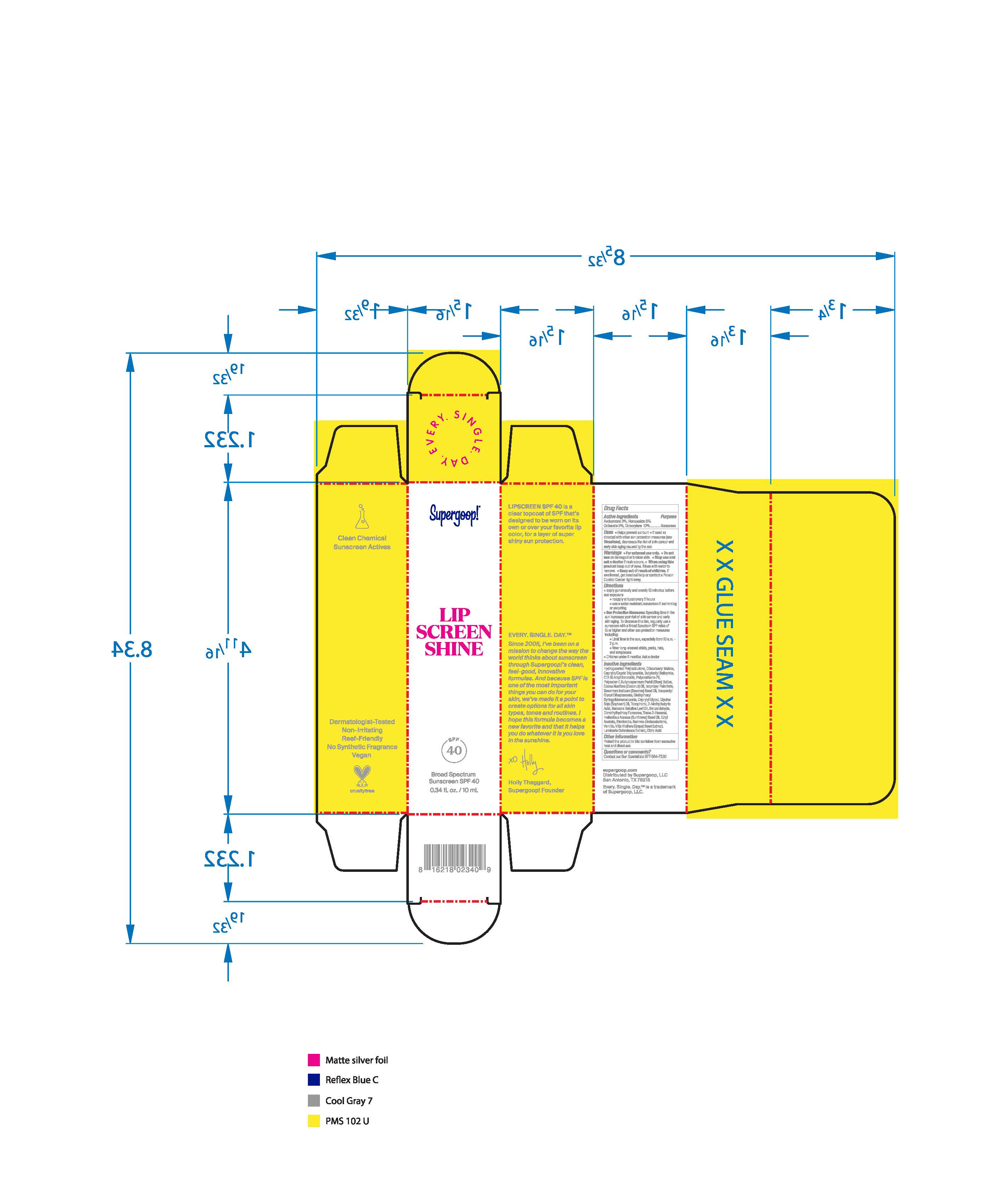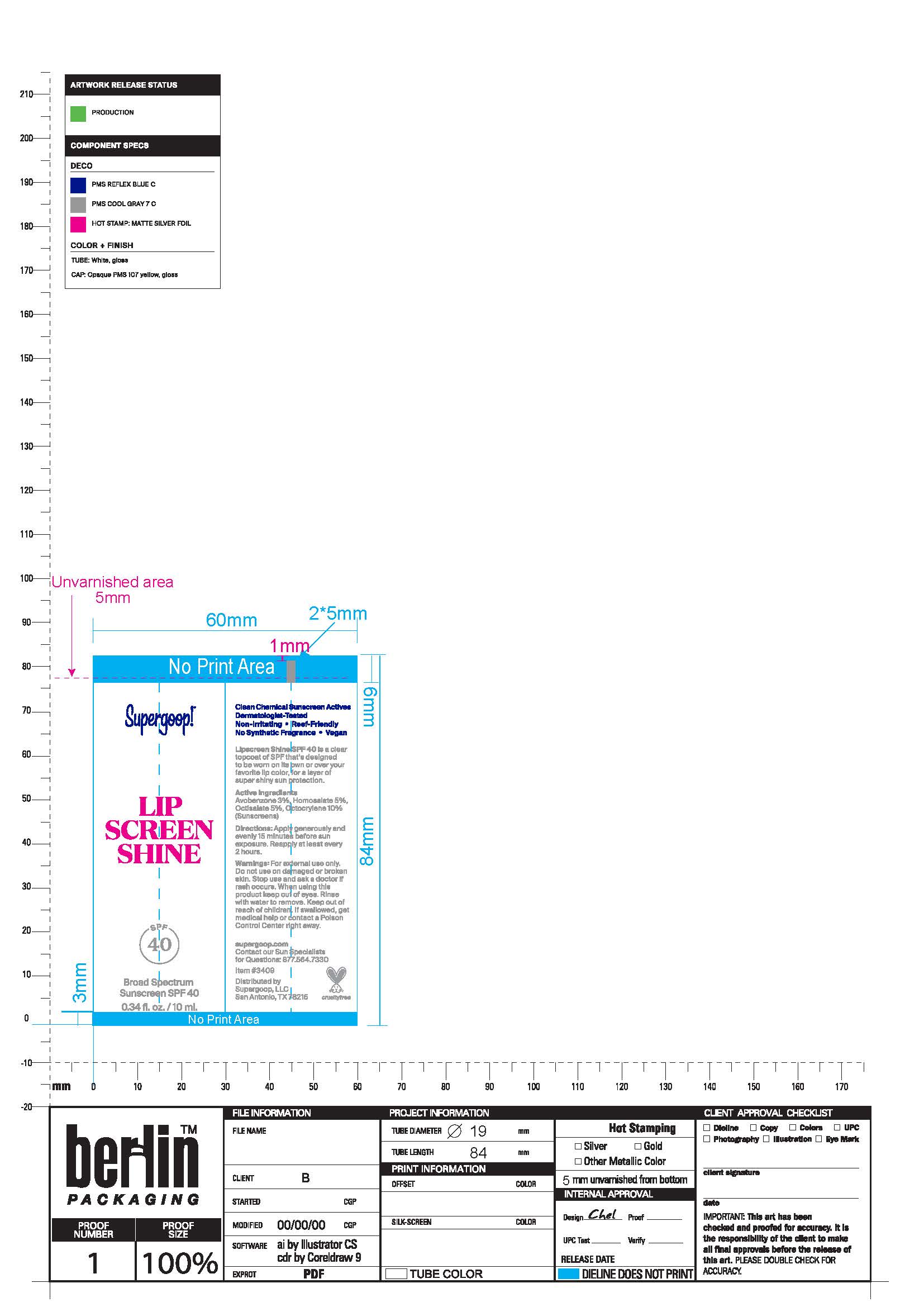 DRUG LABEL: Lip Screen Broad Spectrum SPF 40
NDC: 75936-257 | Form: LIQUID
Manufacturer: Supergoop, LLC
Category: otc | Type: HUMAN OTC DRUG LABEL
Date: 20230711

ACTIVE INGREDIENTS: AVOBENZONE 3 g/100 mL; OCTOCRYLENE 10 g/100 mL; OCTISALATE 5 g/100 mL; HOMOSALATE 5 g/100 mL
INACTIVE INGREDIENTS: ETHYL ACETATE; CAPRYLYL GLYCOL; CITRIC ACID MONOHYDRATE; POLYESTER-7; TOCOPHEROL; DIMETHYLHYDROXY FURANONE; 2-HEXENAL, (2E)-; DIETHYLHEXYL SYRINGYLIDENEMALONATE; LAMINARIA OCHROLEUCA; AGATHOSMA BETULINA LEAF OIL; VANILLIN; 2-METHYLBUTYRIC ACID; SESAME OIL; .GAMMA.-UNDECALACTONE; DIISOSTEARYL MALATE; ALKYL (C12-15) BENZOATE; MEDIUM-CHAIN TRIGLYCERIDES; BUTYLOCTYL SALICYLATE; HYDROGENATED POLYBUTENE (1300 MW); STEVIOSIDE; VITIS VINIFERA SEED; SHEA BUTTER; COCONUT OIL; ISOPROPYL PALMITATE; NEOPENTYL GLYCOL DIHEPTANOATE; SOYBEAN OIL; BENZALDEHYDE

Lip Screen Broad Spectrum SPF 40

ACTIVE INGREDIENT

Avobenzone 3% Sunscreen

Homosalate 5% Sunscreen

Octisalate 5% Sunscreen

Octocrylene 10% Sunscreen

Uses

Helps Prevent Sunburn
If used as directed with other sun protection measures (see Directions), decreases the risk of skin cancer and early skin aging caused by the sun.

Keep out of reach of children. If product is swallowed, get medical help or contact a poison Control Center right away.

Stop use and ask a doctor if rash occurs

Warnings

For external use only

Do not use on damaged or broken skin

When using this product keep out of eyes. Rinse with water to remove

Directions

Apply generously and evenly 15 minutes before sun exposure
Use a water-resistant sunscreen if swimming or sweating
Reapply at least every 2 hours.
Sun Protection Measures Spending time in the sun increases your risk of
skin cancer and early skin aging. To decrease this risk, regularly use a
sunscreen with a Broad-Spectrum SPF value of 15 or higher and other sun
protection measures including: • limit your time in the sun, especially from 10
a.m. – 2 p.m. • wear long-sleeved shirts, pants, hats, and sunglasses •
Children under 6 months of age: ask a doctor.

Inactive Ingredients

Hydrogenated Polyisobutene, Diisostearyl Malate, Caprylic/Capric Triglyceride, Butyloctyl Salicylate, C12-15 Alkyl Benzoate, Polyurethane-79, Polyester-7, Butyrospermum Parkii (Shea) Butter, Cocos Nucifera (Coconut) Oil, Isopropyl Palmitate , Sesamum Inidicum (Sesame) Seed Oil, Neopentyl Glycol Diheptanoate, Diethylhexyl Syringlidenemalonate, Caprylyl Glycol, Glycine Soja (Soybean) Oil, Tocopherol, 2-Methylbutyric Acid, Barosma Betulina Leaf Oil, Benzaldehyde, Dimethylhydroxy Furanone, Trans-2-Hexenal, Helianthus Annuus (Sunflower) Seed Oil, Ethyl Acetate, Stevioside, Gamma-Undecalactone, Vanillin, Vitis Vinifera (Grape) Seed Extract, Laminaria Ochroleuca Extract, Citric Acid

PACKAGE LABEL

Lip Screen

SPF 40

Broad Spectrum SPF 40

0.34 fl. oz. / 10 ml.